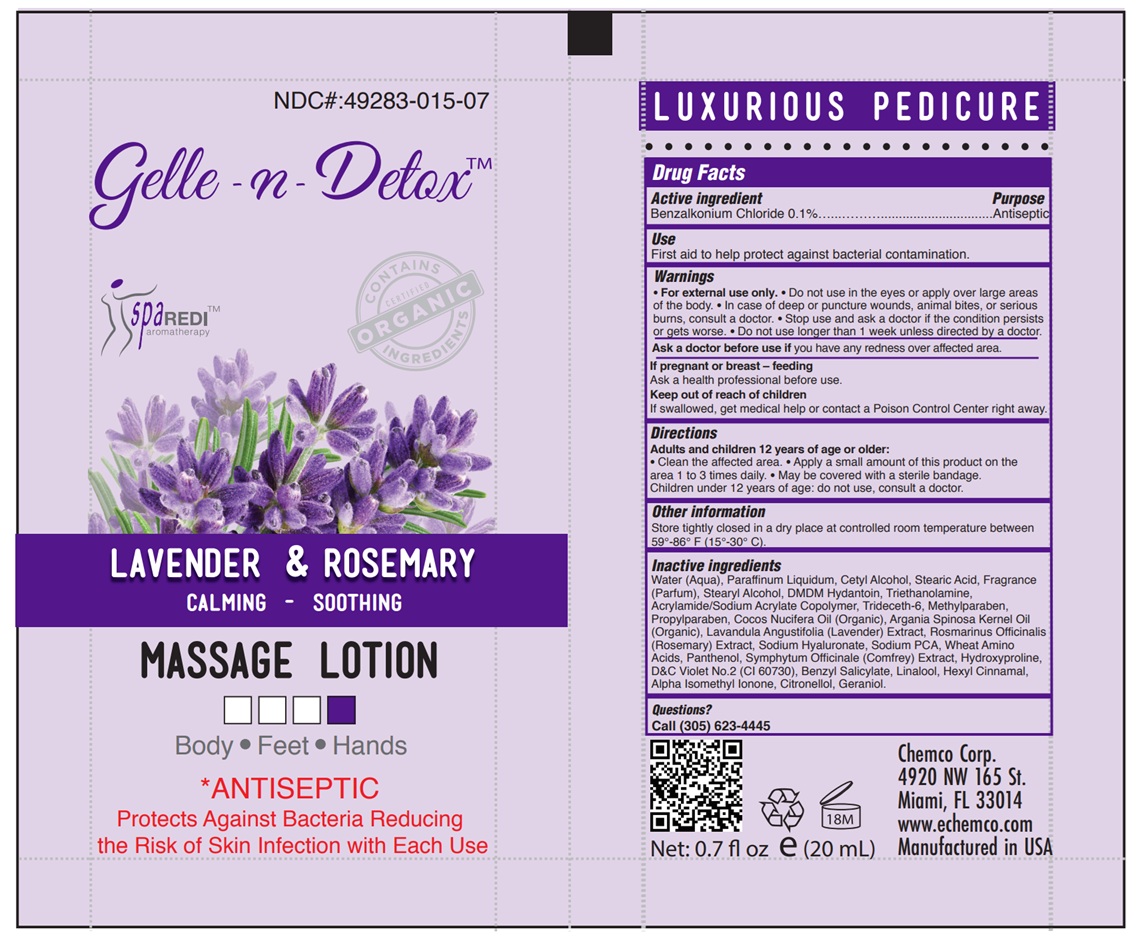 DRUG LABEL: GELLE-N-DETOX - LAVENDER AND ROSEMARY MASSAGE
NDC: 49283-015 | Form: LOTION
Manufacturer: CHEMCO CORPORATION
Category: otc | Type: HUMAN OTC DRUG LABEL
Date: 20251204

ACTIVE INGREDIENTS: BENZALKONIUM CHLORIDE 0.1 g/100 g
INACTIVE INGREDIENTS: CARBOMER HOMOPOLYMER TYPE C; COCONUT OIL; ARGAN OIL; DMDM HYDANTOIN; TROLAMINE; HYALURONATE SODIUM; CETYL ALCOHOL; SYMPHYTUM OFFICINALE WHOLE; LINALOOL, (+/-)-; ISOMETHYL-.ALPHA.-IONONE; STEARYL ALCOHOL; D&C VIOLET NO. 2; BUTYLPHENYL METHYLPROPIONAL; BENZYL SALICYLATE; .ALPHA.-HEXYLCINNAMALDEHYDE; GERANIOL; METHYLPARABEN; PROPYLPARABEN; LAVANDULA ANGUSTIFOLIA WHOLE; STEARIC ACID; TRIDECETH-6; HYDROXYPROLINE; SODIUM PYRROLIDONE CARBOXYLATE; ROSMARINUS OFFICINALIS WHOLE; .BETA.-CITRONELLOL, (R)-; WATER; MINERAL OIL; AMINO ACIDS, WHEAT; PANTHENOL

49283-015-07

ACTIVE INGREDIENT

Benzalkonium Chloride 0.1%

PURPOSE

Antiseptic

Uses

First aid to help protect against bacterial contamination.

WARNINGS

- For external use only.
- Do not use in the eyes or apply over large areas of the body.
- In case of deep or puncture wounds, animal bites, or serious burns, consult a doctor.
- Stop use and ask a doctor if the condition persists or gets worse.
- Do not use longer than 1 week unless directed by a doctor

Ask a doctor before use if you have redness over affected area.

PREGNANCY OR BREAST FEEDING

Ask a health professional before use.

KEEP OUT OF REACH OF CHILDREN

If swallowed, get medical help or contact a Poison Control Center right away.

Directions

Adults and children 12 years of age or older: • Clean the affected area. • Apply a small amount of this product on the area 1 to 3 times daily. • May be covered with a sterile bandage. Children under 12 years of age: do not use, consult a doctor.

OTHER SAFETY INFORMATION

Store tightly closed in a dry place at controlled room temperature between 59°-86° F (15°-30° C).

INACTIVE INGREDIENT

Water (Aqua), Paraffinum Liquidum, Cetyl Alcohol, Stearic Acid, Fragrance (Parfum), Stearyl Alcohol, DMDM Hydantoin, Triethanolamine, Acrylamide/Sodium Acrylate Copolymer, Trideceth-6, Methylparaben, Propylparaben, Cocos Nucifera Oil (Organic), Argania Spinosa Kernel Oil (Organic), Lavandula Angustifolia (Lavender) Extract, Rosmarinus Officinalis (Rosemary) Extract, Sodium Hyaluronate, Sodium PCA, Wheat Amino Acids, Panthenol, Symphytum Officinale (Comfrey) Extract, Hydroxyproline, D&C Violet No.2 (CI 60730), Benzyl Salicylate, Linalool, Hexyl Cinnamal, Alpha Isomethyl Ionone, Citronellol, Geraniol.

QUESTIONS

Call (305) 623-4445